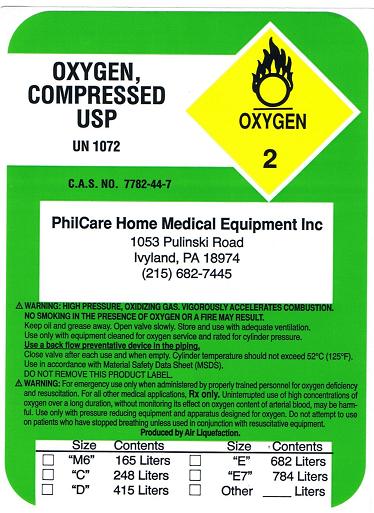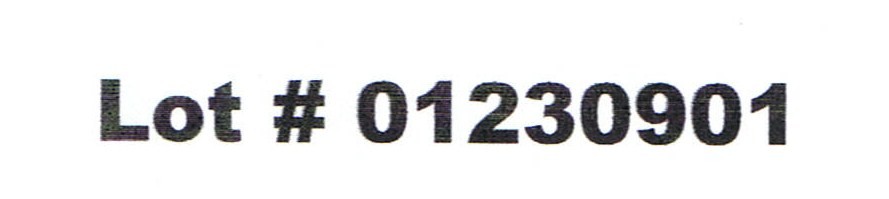 DRUG LABEL: Oxygen
NDC: 64453-0100 | Form: GAS
Manufacturer: PhilCare Home Medical Equipment, Inc.
Category: prescription | Type: HUMAN PRESCRIPTION DRUG LABEL
Date: 20091203

ACTIVE INGREDIENTS: Oxygen 99 L/100 L

Oxygen